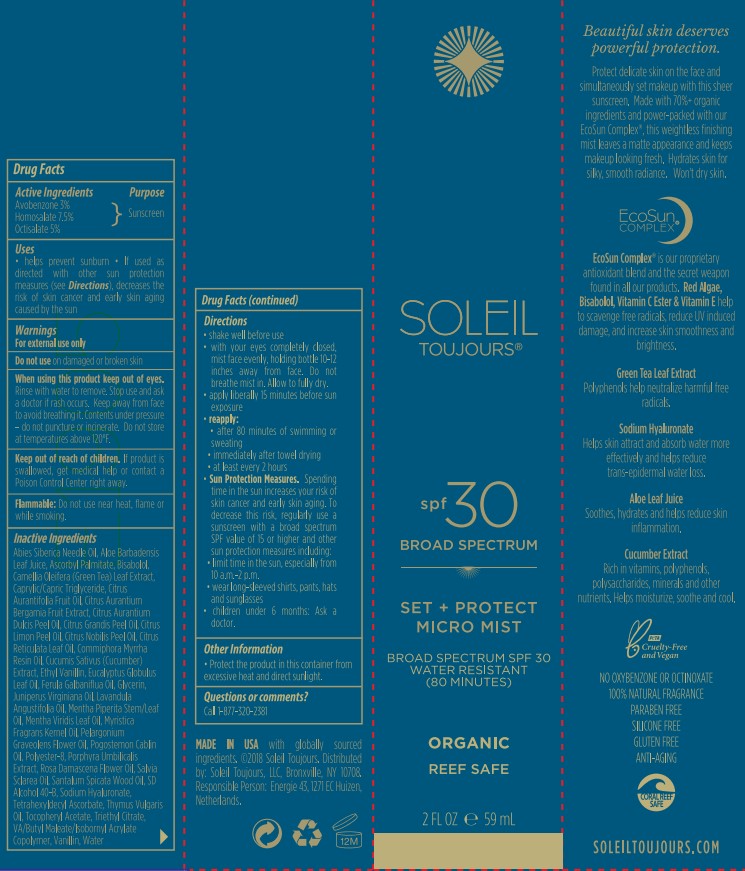 DRUG LABEL: Soleil Toujours
NDC: 58443-0555 | Form: LOTION
Manufacturer: Prime Enterprises Inc.
Category: otc | Type: HUMAN OTC DRUG LABEL
Date: 20220816

ACTIVE INGREDIENTS: OCTISALATE 41.3 mg/1 mL; AVOBENZONE 24.78 mg/1 mL; HOMOSALATE 24.78 mg/1 mL
INACTIVE INGREDIENTS: BERGAMOT OIL; ORANGE PEEL; ALOE VERA LEAF; GLYCERIN; GREEN TEA LEAF; WATER; LEMON OIL, COLD PRESSED; CITRUS NOBILIS; LEVOMENOL; CITRUS AURANTIIFOLIA FRUIT OIL; CITRUS MAXIMA FRUIT RIND OIL; CITRUS RETICULATA LEAF OIL; SPEARMINT OIL; POLYESTER-8 (1400 MW, CYANODIPHENYLPROPENOYL CAPPED); SANTALUM SPICATUM OIL; ALCOHOL; TRIETHYL CITRATE; VANILLIN; MENTHA PIPERITA LEAF; POGOSTEMON CABLIN LEAF OIL; TETRAHEXYLDECYL ASCORBATE; THYME OIL; .ALPHA.-TOCOPHEROL ACETATE; GALBANUM OIL; JUNIPERUS VIRGINIANA OIL; LAVENDER OIL; MYRRH OIL; CUCUMBER; EUCALYPTUS OIL; ROSA DAMASCENA FLOWER OIL; CLARY SAGE OIL; PELARGONIUM GRAVEOLENS FLOWER OIL; ABIES SIBIRICA WHOLE; ETHYL VANILLIN; NUTMEG OIL; PORPHYRA UMBILICALIS; HYALURONATE SODIUM; ASCORBYL PALMITATE; MEDIUM-CHAIN TRIGLYCERIDES

Soleil Toujors Set + Protect Micro Mist Broad Spectrum SPF 30 Sunscreen

Active Ingredients

Avobenzone 3%

Homosalate 7.5%

Octisalate 5%

Purpose

Sunscreen

Uses

- helps prevent sunburn
- If used as directed with other sun protection measures (see Directions), decreases the risk of skin cancer and early skin aging caused by the sun.

Warnings

For external use only

DO NOT USE

Do not us e on damaged or broken skin

When using this product keep out of eyes. Rinse with water to remove.

Stop use and ask a doctor if rash occurs. Keep away from face to avoid breathing it, Contents under pressure - do not puncture or incinerate. Do not store at temperatures above 120ºF.

Keep out of reach of children. If product is swallowed, get medical help or contact a Poison Control Center right away.

Flammable: Do not use near heat,flame or while smoking.

Directions

- shake well before use
- with your eyes completely closed, mist face evenly, holding bottle 10-12 inches away from face. Do not breathe mist in. Allow to fully dry.
- apply liberally 15 minutes before sun exposure
- reapply:
- after 80 minutes of swimming or sweating
- immediately after towel drying
- at least every 2 hours
- Sun Protection Measures. Spending time in the sun increases your risk of skin cancer and early skin aging. To decrease this risk, regularly use a sunscreen with broad spectrum SPF value of 15 or higher and other sun protection measures including:
- limit time in the sun, especially from 10 a.m. – 2 p.m.
- wear long-sleeved shirts, pants, hats, and sunglasses
- children under 6 months: Ask a doctor

INACTIVE INGREDIENT

Abies siberica Needle Oil, Aloe Barbadensis Leaf Juice, Ascorbyl Palmitate, Bisabolol, Camellia Oleifera (Green Tea) Leaf Extract, Caprylic/Capric Triglyceride, Citrus aurantifolia Fruit Oil, Citrus aurantium bergamia Fruit Extract, Citrus aurantium dulcis Peel Oil, Citrus grandis Peel Oil, Citrus limon Peel Oil, Citrus nobilis Peel Oil, Citrus reticulata Leaf Oil, Commiphora myrrha Resin Oil, Cucumis Sativus (Cucumber) Extract, Ethyl Vanillin, Eucalyptus globulus Leaf Oil, Ferula galbaniflua Oil, Glycerin, Juniperus virginiana Oil, Lavandula angustifolia Oil, Mentha piperita Stem/Leaf Oil, Mentha viridis Leaf Oil, Myristica fragrans Kernel Oil, Pelargonium graveolens Flower Oil, Pogostemon cablin Oil, Polyester-8, Porphyra Umbilicalis Extract, Rosa damascena Flower Oil, Salvia sclarea Oil, Santalum spicata Wood Oil, SD Alcohol 40-B, Sodium Hyaluronate, Tetrahexyldecyl Ascorbate, Thymus vulgaris Oil, Tocopheryl Acetate, Triethyl Citrate, VA/Butyl Maleate/Isobornyl Acrylate Copolymer, Vanillin, Water

Other Information

- Protect the product in this container from excessive heat and direct sunlight.

Question or comments?

Call 1-877-320-2381